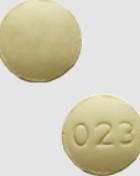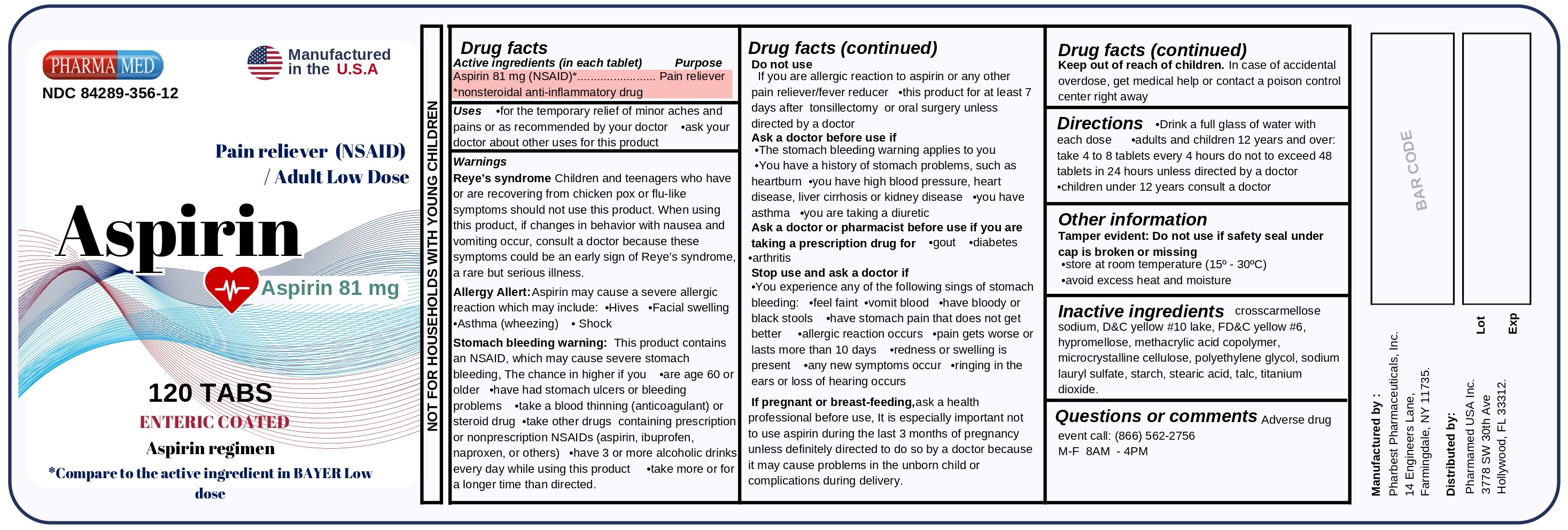 DRUG LABEL: Aspirin 81mg Adult Low Dose
NDC: 84289-356 | Form: TABLET, DELAYED RELEASE
Manufacturer: PHARMAMED USA INC
Category: otc | Type: HUMAN OTC DRUG LABEL
Date: 20240626

ACTIVE INGREDIENTS: ASPIRIN 81 mg/1 1
INACTIVE INGREDIENTS: SODIUM LAURYL SULFATE; CROSCARMELLOSE SODIUM; METHACRYLIC ACID - ETHYL ACRYLATE COPOLYMER (1:2); STARCH, CORN; CELLULOSE, MICROCRYSTALLINE; FD&C YELLOW NO. 6; TALC; TITANIUM DIOXIDE; POLYETHYLENE GLYCOL, UNSPECIFIED; HYPROMELLOSE, UNSPECIFIED; STEARIC ACID; D&C YELLOW NO. 10

Active ingredient (in each tablet)

Aspirin 81mg (NSAID)*

*nonsteroidal anti-inflammatory drug

Purpose

Pain Reliever

Uses

- for the temporary relief of minor aches and pains or as recommended by your doctor. Because of its delayed action, this product may not provide fast relief of headache or other symptoms needing immediate relief.
- ask your doctor about other uses for this product

Warnings

Reye's syndrome: Children and teenagers who have or are recovering from chicken pox or flu-like symptoms should not use this product. When using this product, if changes in behavior with nausea and vomiting occur, consult a doctor because these symptoms could be an early sign of Reye's syndrome, a rare but serious illness.

Allergy alert: Aspirin may cause a severe alergic reaction which may include:

- hives
- asthma (wheezing)
- facial sweling
- shock

Stomach bleeding warning: This product contains an NSAID, which may cause severe stomach bleeding. The chance is higher if you

- are age 60 or older
- have had stomach ulcers or bleeding problems
- take a blood thinning (anticoagulant) or steroid drug
- take other drugs containing prescription or nonprescription NSAIDs (aspirin, ibuprofen, naproxen, or others)
- have 3 or more alcoholic drinks every day while using this product
- take more or for a longer time than directed

Do not use

if you have ever had an allergic reaction to aspirin or any other pain reliever/fever reducer

Ask a doctor before use if

- the stomach bleeding warning applies to you
- you have a history of stomach problems such as heartburn
- you have high blood pressure, heart disease, liver cirrhosis or kidney disease
- you have asthma
- you are taking a diuretic

Ask a doctor or pharmacist before use if you are taking a prescription drug for:

- gout
- diabetes
- arthritis

Stop use and ask a doctor if:

- you experience any of the following signs of stomach bleeding • feel faint •vomit blood •have bloody or black stools •have stomach pain that does not get better
- allergic reaction occurs
- pain gets worse or lasts more than 10 days
- redness or swelling is present
- any new symptoms occur
- ringing in the ears or loss of hearing occurs

These could be signs of a serious condition.

If pregnant or breast-feeding,

ask a health professional before use. It is especially important not to use aspirin during the last 3 months of pregnancy unless definitely directed to do so by a doctor because it may cause problems in the unborn child or complications during delivery.

Keep out of reach of children.

In case of accidental overdose, get medical help or contact a Poison Control Center right away.

Directions

- drink a full glass of water with each dose
- adults and children 12 years and over: take 4 to 8 tablets every 4 hours while symptoms persist. Do not to exceed 48 tablets in 24 hours or as directed by a physician
- children under 12 years: consult a physician

Other information

- Tamper Evident: Do not use if the safety seal under the cap is broken or missing
- store at room temperature (15°-30°C)
- avoid excess heat and moisture

Inactive ingredients

croscarmellose sodium, D&C yelow# 10 lake, FD&C yellow #6, hypromellose, methacrylic acid copolymer, microcrystalline cellulose, polyethylene glycol, sodium lauryl sulfate, starch, stearic acid, talc, titanium dioxide.

Questions? Adverse drug event call:

(866) 562-2756

Package Label Principal Display Panel

PHARMAMED

NDC 84289-356-12

Manufactured in the U.S.A

Pain Reliever (NSAID) / Adult Low Dose

Aspirin

Aspirin 81mg

120 TABS

ENTERIC COATED

Aspirin Regimen

*Compare to the active ingredient in BAYER Low dose